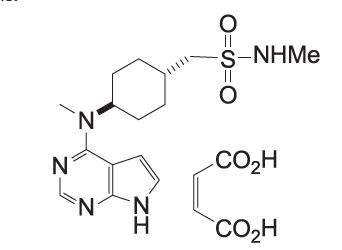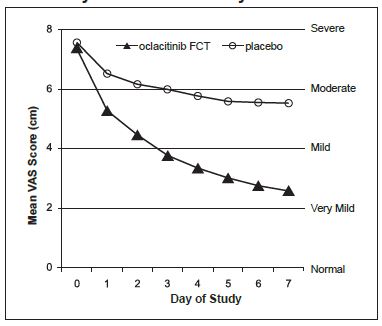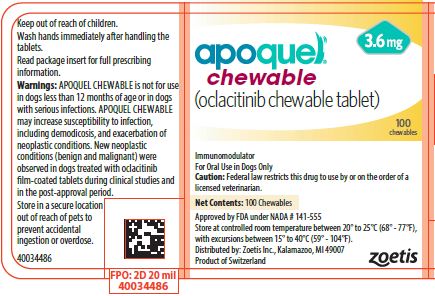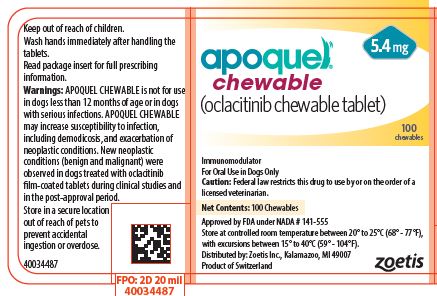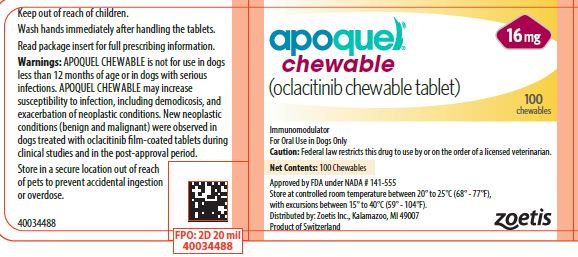 DRUG LABEL: Apoquel Chewable
NDC: 54771-4322 | Form: TABLET, CHEWABLE
Manufacturer: Zoetis Inc.
Category: animal | Type: PRESCRIPTION ANIMAL DRUG LABEL
Date: 20251016

ACTIVE INGREDIENTS: OCLACITINIB MALEATE 3.6 mg/1 1

apoquel chewable

apoquel®
chewable
(oclacitinib chewable tablet)
Immunomodulator
For oral use in dogs only

Caution

Federal (USA) Law restricts this drug to use by or on the order of a licensed veterinarian.

Description

APOQUEL CHEWABLE (oclacitinib chewable tablet) is a synthetic Janus Kinase (JAK) inhibitor. The chemical composition of oclacitinib maleate is N-methyl-1-[trans-4-(methyl-7H-pyrrolo[2,3-d]pyrimidin-4-ylamino) cyclohexyl]methanesulfonamide (2Z)-2-butenedioate.

The chemical structure of oclacitinib maleate is:

Indications

Control of pruritus associated with allergic dermatitis and control of atopic dermatitis in dogs at least 12 months of age.

Dosage and Administration

The dose of APOQUEL CHEWABLE (oclacitinib chewable tablet) is 0.18 to 0.27 mg oclacitinib/lb (0.4 to 0.6 mg oclacitinib/kg) body weight, administered orally, twice daily for up to 14 days, and then administered once daily for maintenance therapy.

Dosing Chart
Weight Range (in lb) |  | Weight Range (in Kg) |  |  | Number of Tablets to be Administered
Low | High | Low | High |  | 3.6 mg Tablets | 5.4 mg Tablets | 16 mg Tablets
6.6 | 9.9 | 3.0 | 4.4 |  | 0.5 | - | -
10.0 | 14.9 | 4.5 | 5.9 |  | - | 0.5 | -
15.0 | 19.9 | 6.0 | 8.9 |  | 1 | - | -
20.0 | 29.9 | 9.0 | 13.4 |  | - | 1 | -
30.0 | 44.9 | 13.5 | 19.9 |  | - | - | 0.5
45.0 | 59.9 | 20.0 | 26.9 |  | - | 2 | -
60.0 | 89.9 | 27.0 | 39.9 |  | - | - | 1
90.0 | 129.9 | 40.0 | 54.9 |  | - | - | 1.5
130.0 | 175.9 | 55.0 | 80.0 |  | - | - | 2

Warnings

APOQUEL CHEWABLE is not for use in dogs less than 12 months of age (see Animal Safety).
APOQUEL CHEWABLE modulates the immune system.
APOQUEL CHEWABLE is not for use in dogs with serious infections.
APOQUEL CHEWABLE may increase susceptibility to infection, including demodicosis, and exacerbation of neoplastic conditions (see Precautions, Adverse Reactions, Post-Approval Experience and Animal Safety).

New neoplastic conditions (benign and malignant) were observed in dogs treated with oclacitinib film-coated tablets (FCT) during clinical studies and have been reported in the post-approval period (see Adverse Reactions and Post-Approval Experience).
Consider the risks and benefits of treatment prior to initiating APOQUEL CHEWABLE in dogs with a history of recurrent serious infections or recurrent demodicosis or neoplasia (see Adverse Reactions, Post-Approval Experience, and Animal Safety).
Keep APOQUEL CHEWABLE in a secure location out of reach of dogs, cats, and other animals to prevent accidental ingestion or overdose.

Human Warnings

This product is not for human use. Keep this and all drugs out of reach of children. For use in dogs only. Wash hands immediately after handling the tablets. In case of accidental eye contact, flush immediately with water or saline for at least 15 minutes and then seek medical attention. In case of accidental ingestion, seek medical attention immediately.

Precautions

Dogs receiving APOQUEL CHEWABLE should be monitored for the development of infections, including demodicosis, and neoplasia.
The use of APOQUEL CHEWABLE has not been evaluated in combination with glucocorticoids, cyclosporine, or other systemic immunosuppressive agents.
APOQUEL CHEWABLE is not for use in breeding dogs, or pregnant or lactating bitches.

Adverse Reactions

The safety of APOQUEL CHEWABLE was established by pharmacokinetic data comparing oclacitinib film-coated tablets to APOQUEL CHEWABLE (see Clinical Pharmacology).

Control of Atopic Dermatitis

In a masked field study to assess the effectiveness and safety of oclacitinib for the control of atopic dermatitis in dogs, 152 dogs treated with oclacitinib FCT and 147 dogs treated with placebo (vehicle control) were evaluated for safety. The majority of dogs in the placebo group withdrew from the 112-day study by Day 16. Adverse reactions reported (and percent of dogs affected) during Days 0-16 included diarrhea (4.6% oclacitinib FCT, 3.4% placebo), vomiting (3.9% oclacitinib FCT, 4.1% placebo), anorexia (2.6% oclacitinib FCT, 0% placebo), new cutaneous or subcutaneous lump (2.6% oclacitinib FCT, 2.7% placebo), and lethargy (2.0% oclacitinib FCT, 1.4% placebo). In most cases, diarrhea, vomiting, anorexia, and lethargy spontaneously resolved with continued dosing. Dogs on oclacitinib FCT had decreased leukocytes (neutrophil, eosinophil, and monocyte counts) and serum globulin, and increased cholesterol and lipase compared to the placebo group but group means remained within the normal range. Mean lymphocyte counts were transiently increased at Day 14 in the oclacitinib FCT group.
Dogs that withdrew from the masked field study could enter an unmasked study where all dogs received oclacitinib FCT. Between the masked and unmasked study, 283 dogs received at least one dose of oclacitinib FCT. Of these 283 dogs, two dogs were withdrawn from study due to suspected treatment-related adverse reactions: one dog that had an intense flare-up of dermatitis and severe secondary pyoderma after 19 days of oclacitinib FCT administration, and one dog that developed generalized demodicosis after 28 days of oclacitinib FCT administration. Two other dogs on oclacitinib FCT were withdrawn from study due to suspected or confirmed malignant neoplasia and subsequently euthanized, including one dog that developed signs associated with a heart base mass after 21 days of oclacitinib FCT administration, and one dog that developed a Grade III mast cell tumor after 60 days of oclacitinib FCT administration.
One of the 147 dogs in the placebo group developed a Grade I mast cell tumor and was withdrawn from the masked study. Additional dogs receiving oclacitinib FCT were hospitalized for diagnosis and treatment of pneumonia (one dog), transient bloody vomiting and stool (one dog), and cystitis with urolithiasis (one dog).
In the 283 dogs that received oclacitinib FCT, the following additional clinical signs were reported after beginning oclacitinib FCT (percentage of dogs with at least one report of the clinical sign as a non-pre-existing finding): pyoderma (12.0%), non-specified dermal lumps (12.0%), otitis (9.9%), vomiting (9.2%), diarrhea (6.0%), histiocytoma (3.9%), cystitis (3.5%), anorexia (3.2%), lethargy (2.8%), yeast skin infections (2.5%), pododermatitis (2.5%), lipoma (2.1%), polydipsia (1.4%), lymphadenopathy (1.1%), nausea (1.1%), increased appetite (1.1%), aggression (1.1%), and weight loss (0.7).

Control of Pruritus Associated with Allergic Dermatitis

In a masked field study to assess the effectiveness and safety of oclacitinib for the control of pruritus associated with allergic dermatitis in dogs, 216 dogs treated with oclacitinib FCT and 220 dogs treated with placebo (vehicle control) were evaluated for safety. During the 30-day study, there were no fatalities and no adverse reactions requiring hospital care. Adverse reactions reported (and percent of dogs affected) during Days 0-7 included diarrhea (2.3% oclacitinib FCT, 0.9% placebo), vomiting (2.3% oclacitinib FCT, 1.8% placebo), lethargy (1.8% oclacitinib FCT, 1.4% placebo), anorexia (1.4% oclacitinib FCT, 0% placebo), and polydipsia (1.4% oclacitinib FCT, 0% placebo). In most of these cases, signs spontaneously resolved with continued dosing. Five oclacitinib FCT group dogs were withdrawn from study because of: darkening areas of skin and fur (1 dog); diarrhea (1 dog); fever, lethargy and cystitis (1 dog); an inflamed footpad and vomiting (1 dog); and diarrhea, vomiting, and lethargy (1 dog). Dogs in the oclacitinib FCT group had a slight decrease in mean white blood cell counts (neutrophil, eosinophil, and monocyte counts) that remained within the normal reference range. Mean lymphocyte count for dogs in the oclacitinib FCT group increased at Day 7, but returned to pretreatment levels by study end without a break in oclacitinib FCT administration. Serum cholesterol increased in 25% of oclacitinib FCT group dogs, but mean cholesterol remained within the reference range.

Continuation Field Study

After completing oclacitinib FCT field studies, 239 dogs enrolled in an unmasked (no placebo control), continuation therapy study receiving oclacitinib FCT for an unrestricted period of time. Mean time on this study was 372 days (range 1 to 610 days). Of these 239 dogs, one dog developed demodicosis following 273 days of oclacitinib FCT administration. One dog developed dermal pigmented viral plaques following 266 days of oclacitinib FCT administration. One dog developed a moderately severe bronchopneumonia after 272 days of oclacitinib FCT administration; this infection resolved with antimicrobial treatment and temporary discontinuation of oclacitinib FCT. One dog was euthanized after developing abdominal ascites and pleural effusion of unknown etiology after 450 days of oclacitinib FCT administration. Six dogs were euthanized because of suspected malignant neoplasms: including thoracic metastatic, abdominal metastatic, splenic, frontal sinus, and intracranial neoplasms, and transitional cell carcinoma after 17, 120, 175, 49, 141, and 286 days of oclacitinib FCT administration, respectively. Two dogs each developed a Grade II mast cell tumor after 52 and 91 days of oclacitinib FCT administration, respectively. One dog developed low grade B-cell lymphoma after 392 days of oclacitinib FCT administration. Two dogs each developed an apocrine gland adenocarcinoma (one dermal, one anal sac) after approximately 210 and 320 days of oclacitinib FCT administration, respectively. One dog developed a low grade oral spindle cell sarcoma after 320 days of oclacitinib FCT administration.

Post-Approval Experience (2020)

The following adverse events are based on post-approval adverse drug experience reporting for oclacitinib FCT. Not all adverse events are reported to FDA/CVM. It is not always possible to reliably estimate the adverse event frequency or establish a causal relationship to product exposure using these data.
The following adverse events reported in dogs are listed in decreasing order of reporting frequency.
Vomiting, lethargy, anorexia, diarrhea, elevated liver enzymes, dermatitis (i.e. crusts, pododermatitis, pyoderma), seizures, polydipsia, and demodicosis.
Benign, malignant, and unclassified neoplasms, dermal masses (including papillomas and histiocytomas), lymphoma and other cancers have been reported.
Death (including euthanasia) has been reported.

Contact Information

To report suspected adverse events, for technical assistance or to obtain a copy of the Safety Data Sheet, contact Zoetis Inc. at 1-888-963-8471 or www.zoetis.com.
For additional information about adverse drug experience reporting for animal drugs, contact FDA at 1-888-FDA-VETS or online at www.fda.gov/reportanimalae.

Clinical Pharmacology

Mechanism of action

Oclacitinib inhibits the function of a variety of pruritogenic cytokines and pro-inflammatory cytokines, as well as cytokines involved in allergy that are dependent on JAK1 or JAK3 enzyme activity. It has little effect on cytokines involved in hematopoiesis that are dependent on JAK2. Oclacitinib is not a corticosteroid or an antihistamine.

Pharmacokinetics

A pharmacokinetic study was conducted to compare the bioavailability of APOQUEL CHEWABLE with oclacitinib FCT. Bioequivalence (BE) was demonstrated for the extent of exposure between APOQUEL CHEWABLE and oclacitinib FCT with the geometric mean ratio for the area under the curve from zero to the last sampling time point [AUC0-t(last)] of 1.03 and the 90% confidence interval (CI) within the acceptable range of 0.80 to 1.25. However, BE was not demonstrated for the maximum concentration (Cmax), with the geometric mean ratio of 0.86 and 90% CI of 0.78 to 0.95, outside the acceptable range of 0.8 to 1.25. Based on simulations, in accordance with the dosage regimen, the small differences in Cmax values between APOQUEL CHEWABLE and oclacitinib FCT after the first dose are likely to be minimal at steady-state.
In dogs, oclacitinib is rapidly and well absorbed following oral administration, with mean time to peak plasma concentrations (Tmax) of less than 2 hours. Following oral administration of a single 5.4 mg APOQUEL CHEWABLE to 42 dogs, the mean Cmax was 292 ng/mL and the mean area under the plasma concentration-time curve from 0 and extrapolated to infinity (AUC0-inf) was 2570 ng·hr/mL.
Oclacitinib has low protein binding with 66.3-69.7% bound in fortified canine plasma at nominal concentrations ranging from 10-1000 ng/mL. The apparent mean (95% CL)volume of distribution at steady-state was942 (870, 1014) mL/kg body weight.
Mean (95% CL) total body oclacitinib clearance from plasma was low – 316 (237, 396)mL/h/kg body weight (5.3 mL/min/kgbody weight). Following intravenous and oraladministration, the terminal half-life appearedsimilar with mean values of 3.5 (2.2, 4.7) and4.1 (3.1, 5.2) hours, respectively.
Oclacitinib is metabolized in the dog to multiple metabolites and one major oxidative metabolite was identified in plasma and urine. Overall the major clearance route is metabolism with minor contributions from renal and biliary elimination. Inhibition of canine cytochrome P450 enzymes by oclacitinib is minimal; the inhibitory concentrations (IC50s) are 50 fold greater than the observed Cmax values at the use dose.

Effectiveness

The effectiveness of APOQUEL CHEWABLE was established by pharmacokinetic data comparing oclacitinib FCT to APOQUEL CHEWABLE (see Clinical Pharmacology).

Bioequivalence was not met for the lower 90% CI of the maximum concentration (Cmax), which may delay the speed of onset of effectiveness of APOQUEL CHEWABLE at the first dose or when transitioning from the oclacitinib FCT.

Control of Atopic Dermatitis

A double-masked, 112-day, controlled study was conducted at 18 U.S. veterinary hospitals. The study enrolled 299 client-owned dogs with atopic dermatitis. Dogs were randomized to treatment with oclacitinib FCT (152 dogs: tablets administered at a dose of 0.4-0.6 mg/kg per dose twice daily for 14 days and then once daily) or placebo (147 dogs: vehicle control, tablets administered on the same schedule). During the study, dogs could not be treated with other drugs that could affect the assessment of effectiveness, such as corticosteroids, anti-histamines, or cyclosporine. Treatment success for pruritus for each dog was defined as at least a 2 cm decrease from baseline on a 10 cm visual analog scale (VAS) in pruritus, assessed by the Owner, on Day 28. Treatment success for skin lesions was defined as a 50% decrease from the baseline Canine Atopic Dermatitis Extent and Severity Index (CADESI) score, assessed by the Veterinarian, on Day 28. The estimated proportion of dogs with Treatment Success in Owner-assessed pruritus VAS score and in Veterinarian-assessed CADESI score was greater and significantly different for the oclacitinib FCT group compared to the placebo group.

Estimated Proportion of Dogs with Treatment Success, Atopic Dermatitis
Effectiveness Parameter | oclacitinib FCT | Placebo | P-value
Owner-Assessed Pruritus VAS | 0.66 (n = 131) | 0.04 (n = 133) | p<0.0001
Veterinarian-Assessed CADESI | 0.49 (n = 134) | 0.04 (n = 134) | p<0.0001

Compared to the placebo group, mean Owner-assessed pruritus VAS scores (on Days 1, 2, 7, 14, and 28) and Veterinarian-assessed CADESI scores (on Days 14 and 28) were lower (improved) in dogs in the oclacitinib FCT group. By Day 30, 86% (127/147) of the placebo group dogs and 15% (23/152) of the oclacitinib FCT group dogswithdrew from the masked study because of worsening clinical signs, and had the option to enroll in an unmasked study and receive oclacitinib FCT. For dogs that continued oclacitinib FCT treatment beyond one month, the mean Owner-assessed pruritus VAS scores and Veterinarian-assessed CADESI scores continued to improve through study end at Day 112.

Control of Pruritus Associated with Allergic Dermatitis

A double-masked, 30-day, controlled study was conducted at 26 U.S. veterinary hospitals. The study enrolled 436 client-owned dogs with a history of allergic dermatitis attributed to one or more of the following conditions: atopic dermatitis, flea allergy, food allergy, contact allergy, and other/unspecified allergic dermatitis. Dogs were randomized to treatment with oclacitinib FCT (216 dogs: tablets administered at a dose of 0.4-0.6 mg/kg twice daily) or placebo (220 dogs: vehicle control, tablets administered twice daily). During the study, dogs could not be treated with other drugs that could affect the assessment of pruritus or dermal inflammation such as corticosteroids, anti-histamines, or cyclosporine. Treatment success for each dog was defined as at least a 2 cm decrease from baseline on a 10 cm visual analog scale (VAS) in pruritus, assessed by the Owner, on at least 5 of the 7 evaluation days. The estimated proportion of dogs with Treatment Success was greater and significantly different for the oclacitinib FCT group compared to the placebo group.

Owner-Assessed Pruritus VAS Treatment Success, Allergic Dermatitis
Effectiveness Parameter | oclacitinib FCT (n = 203) | Placebo (n = 204) | P-value
Estimated Proportion of Dogs with Treatment Success | 0.67 | 0.29 | p<0.0001

After one week of treatment, 86.4% of oclacitinib FCT group dogs compared with 42.5% of placebo group dogs had achieved a 2 cm reduction on the 10 cm Owner-assessed pruritus VAS. On each of the 7 days, mean Owner-assessed pruritus VAS scores were lower in dogs in the oclacitinib FCT group (see Figure 1). Veterinarians used a 10 cm VAS scale to assess each dog’s dermatitis. After one week of treatment, the mean Veterinarian-assessed VAS dermatitis score for the dogs in the oclacitinib FCT group was lower at 2.2 cm (improved from a baseline value of 6.2 cm) compared with the placebo group mean score of 4.9 cm (from a baseline value of 6.2 cm). For dogs that continued oclacitinib FCT treatment beyond one week, the Veterinarian-assessed dermatitis scores continued to improve through study end at Day 30.

Figure 1: Owner Assessed Pruritus VAS Scores by treatment for Days 0-7

Palatability

In a well-controlled U.S. field study, in which 1,662 doses of APOQUEL CHEWABLE were administered to 120 dogs, a total of 1,522 doses (91.6%) were accepted voluntarily within 5 minutes. Of the 140 doses unconsumed after 5 minutes, 134 (8%) were consumed with assistance (with food treats or by pilling), and 6 (0.4%) doses were refused.

Animal Safety

Margin of Safety in 12 Month Old Dogs

Oclacitinib maleate was administered to healthy, one-year-old Beagle dogs twice daily for 6 weeks, followed by once daily for 20 weeks, at 0.6 mg/kg (1X maximum exposure dose, 8 dogs), 1.8 mg/kg (3X, 8 dogs), and 3.0 mg/kg (5X, 8 dogs) oclacitinib for 26 weeks. Eight dogs received placebo (empty gelatin capsule) at the same dosage schedule. Clinical observations that were considered likely to be related to oclacitinib maleate included papillomas and a dose-dependent increase in the number and frequency of interdigital furunculosis (cysts) on one or more feet during the study. Additional clinical observations were primarily related to the interdigital furunculosis and included dermatitis (local alopecia, erythema, abrasions, scabbing/crusts, and edema of feet) and lymphadenopathy of peripheral nodes. Microscopic findings considered to be oclacitinib maleate-related included decreased cellularity (lymphoid) in Gut-Associated Lymphoid Tissue (GALT), spleen, thymus, cervical and mesenteric lymph node; and decreased cellularity of sternal and femoral bone marrow. Lymphoid hyperplasia and chronic active inflammation was seen in lymph nodes draining feet affected with interdigital furunculosis. Five oclacitinib maleate-treated dogs had microscopic evidence of mild interstitial pneumonia.

Clinical pathology findings considered to be oclacitinib maleate-related included mild, dose-dependent reduction in hemoglobin, hematocrit, and reticulocyte counts during the twice daily dosing period with decreases in the leukocyte subsets of lymphocytes, eosinophils, and basophils. Total proteins were decreased over time primarily due to the albumin fraction.

Vaccine Response Study

An adequate immune response (serology) to killed rabies (RV), modified live canine distemper virus (CDV), and modified live canine parvovirus (CPV) vaccination was achieved in eight 16-week old vaccine naïve puppies that were administered oclacitinib maleate at 1.8 mg/kg oclacitinib (3X maximum exposure dose) twice daily for 84 days. For modified live canine parainfluenza virus (CPI), < 80% (6 of 8) of the dogs achieved adequate serologic response. Clinical observations that were considered likely to be related to oclacitinib maleate treatment included enlarged lymph nodes, interdigital furunculosis, cysts, and pododermatitis. One oclacitinib maleate-treated dog (26-weeks-old) was euthanized on Day 74 after physical examination revealed the dog to be febrile, lethargic, with pale mucous membranes and frank blood in stool. Necropsy revealed pneumonia of short duration and evidence of chronic lymphadenitis of mesenteric lymph nodes. During the three month recovery phase to this study, one oclacitinib maleate-treated dog (32-weeks old) was euthanized on Day 28 due to clinical signs which included enlarged prescapular lymph nodes, bilateral epiphora, lethargy, mild dyspnea, and fever. The dog showed an elevated white blood cell (WBC) count. Necropsy revealed lesions consistent with sepsis secondary to immunosuppression. Bone marrow hyperplasia was consistent with response to sepsis.

Margin of Safety in 6 Month Old Dogs

A margin of safety study in 6-month-old dogs was discontinued after four months due to the development of bacterial pneumonia and generalized demodex mange infections in dogs in the high dose (3X and 5X) treatment groups, dosed at 1.8 and 3.0 mg/kg oclacitinib twice daily, for the entire study.

Storage Conditions

APOQUEL CHEWABLE should be stored at controlled room temperature between 20° to 25°C (68° to 77°F) with excursions between 15° to 40°C (59° to 104°F). Remaining half tablets should be stored in the original package and used for the next dose.

How Supplied

APOQUEL CHEWABLE tablets contain 3.6 mg, 5.4 mg, or 16 mg of oclacitinib as oclacitinib maleate per tablet. Each strength chewable tablets are packaged in 250 count bottles, in a 10 count blister pack and in a 100 count 10 x 10 blister pack. Each chewable tablet is pentagon shaped, scored on both sides and have a dose descriptor (S S, M M or L L) debossed on one face across the score line. The S (small), M (medium) and L (large) markings correspond to the tablet strengths of 3.6 mg, 5.4 mg and 16 mg respectively.

Approved by FDA under NADA # 141-555
Distributed by:
Zoetis Inc.
Kalamazoo, MI 49007
Revised: July 2025
40053726

PRINCIPAL DISPLAY PANEL - 3.6 mg Tablet Bottle Label

40034486

PRINCIPAL DISPLAY PANEL - 5.4 mg Tablet Bottle Label

40034487

PRINCIPAL DISPLAY PANEL - 16 mg Tablet Bottle Label

40034488